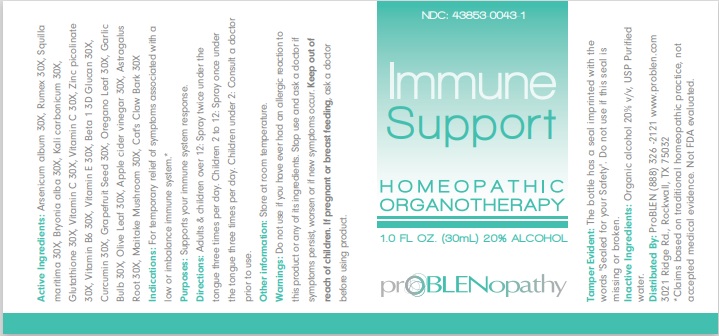 DRUG LABEL: Immune Support
NDC: 43853-0043 | Form: LIQUID
Manufacturer: ProBLEN
Category: homeopathic | Type: HUMAN OTC DRUG LABEL
Date: 20221130

ACTIVE INGREDIENTS: ARSENIC TRIOXIDE 30 [hp_X]/30 mL; RUMEX CRISPUS ROOT 30 [hp_X]/30 mL; DRIMIA MARITIMA BULB 30 [hp_X]/30 mL; BRYONIA ALBA ROOT 30 [hp_X]/30 mL; POTASSIUM CARBONATE 30 [hp_X]/30 mL; GLUTATHIONE 30 [hp_X]/30 mL; ASCORBIC ACID 30 [hp_X]/30 mL; ZINC PICOLINATE 30 [hp_X]/30 mL; PYRIDOXINE 30 [hp_X]/30 mL; .ALPHA.-TOCOPHEROL 30 [hp_X]/30 mL; CURDLAN 30 [hp_X]/30 mL; CURCUMIN 30 [hp_X]/30 mL; CITRUS PARADISI SEED 30 [hp_X]/30 mL; OREGANO 30 [hp_X]/30 mL; GARLIC 30 [hp_X]/30 mL; OLEA EUROPAEA LEAF 30 [hp_X]/30 mL; APPLE CIDER VINEGAR 30 [hp_X]/30 mL; ASTRAGALUS PROPINQUUS ROOT 30 [hp_X]/30 mL; MAITAKE 30 [hp_X]/30 mL; BIANCAEA DECAPETALA ROOT BARK 30 [hp_X]/30 mL; ASCORBYL PALMITATE 30 [hp_X]/30 mL
INACTIVE INGREDIENTS: WATER; ALCOHOL

Immune Support

ACTIVE INGREDIENT

Active Ingredients: Arsenicum album 30X, Rumex 30X, Squilla maritima 30X, Bryonia alba 30X, Kali carbonicum 30X, Glutathione 30X,

Vitamin C 30X, Vitamin C 30X, Zinc picolinate 30X, Vitamin B6 30X, Vitamin E 30X, Beta 1 3D Glucan 30X, Curcumin 30X, Grapefruit Seed 30X, Oregano Leaf 30X, Garlic Bulb 30X, Olive Leaf 30X, Apple cider vinegar 30X, Astragalus Root 30X, Maitake Mushroom 30X, Cat's Claw Bark 30X

*Claims based on traditional homeopathic practice, not accepted medical evidence. Not FDA evaluated.

INDICATIONS AND USAGE

Indications: For temporary relief of symptoms associated with a low or imbalance immune system.*

WARNINGS

Warnings: Do not use if you have ever had an allergic reaction to this product or any of its ingredients. Stop use and ask a doctor if symptoms persist, worsen or if new symptoms occur.

Keep out of reach of children. If pregnant or breast feeding, ask a doctor before using product.

DOSAGE AND ADMINISTRATION

Directions: Adults & children over 12: Spray twice under the tongue three times per day. Children 2 to 12: Spray once under the tongue three times per day. Children under 2: Consult a doctor prior to use.

Other information: Store at room temperature.

Tamper Evident: The bottle has a seal imprinted with the words "Sealed for your Safety". Do not use if this seal is missing or broken.

INACTIVE INGREDIENT

Inactive Ingredients: Organic alcohol 20% v/v, USP Purified water.

QUESTIONS

Distributed By: ProBLEN (888) 326 - 2121

www.problen.com 3021 Ridge Rd., Rockwall, TX 75032

PACKAGE LABEL

NDC: 43853-0043-1

Immune Support

HOMEOPATHIC ORGANOTHERAPY

1.0 FL OZ. (30mL) 20% ALCOHOL

prOBLENopathy

PURPOSE

Purposes: Supports your immune system response